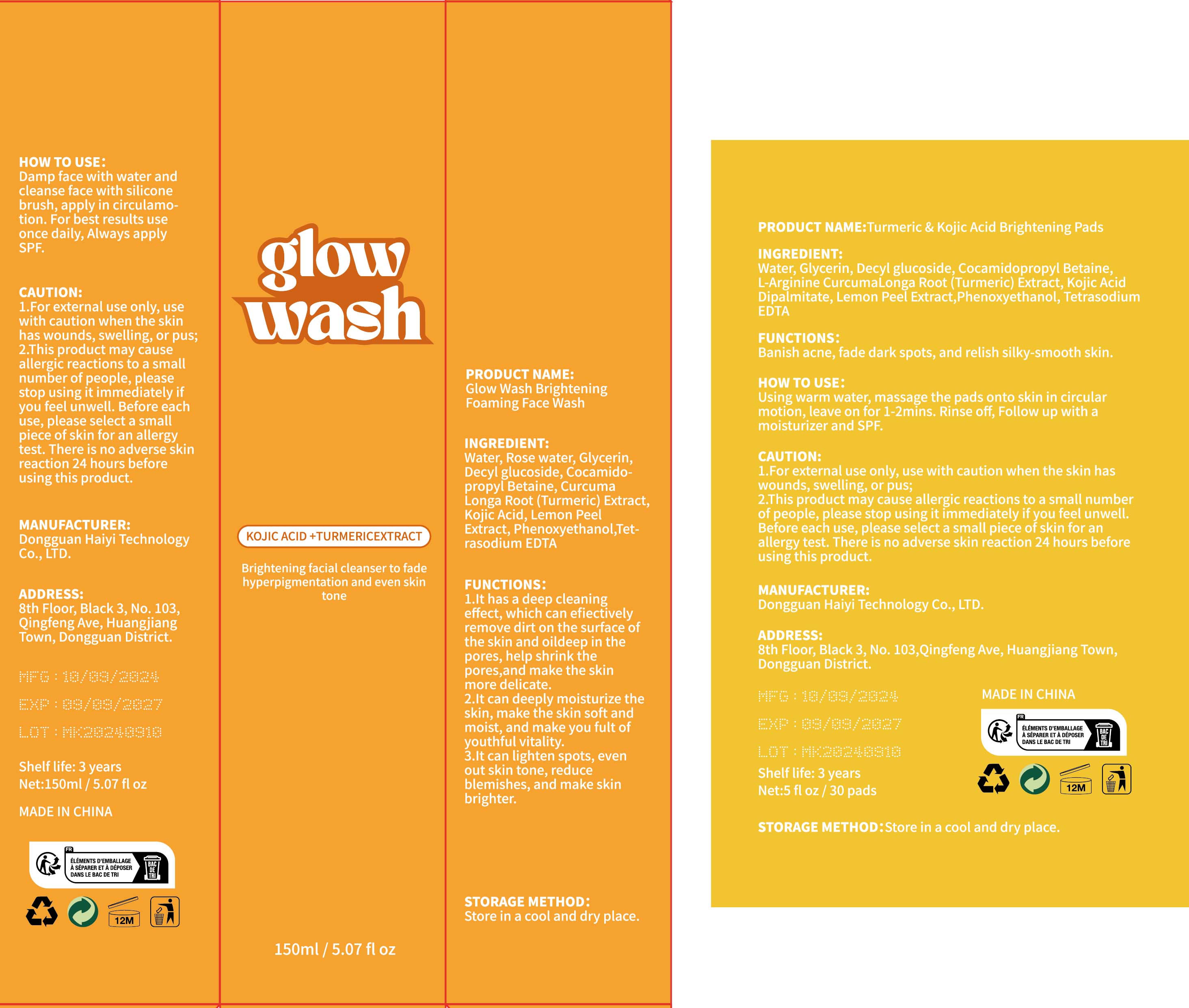 DRUG LABEL: Turmeric Skin Care Kit
NDC: 84732-061 | Form: LIQUID
Manufacturer: Dongguan Haiyi Technology Co.,Ltd.
Category: otc | Type: HUMAN OTC DRUG LABEL
Date: 20241023

ACTIVE INGREDIENTS: ROSA X DAMASCENA FLOWER OIL 1 mg/150 mL
INACTIVE INGREDIENTS: PHENOXYETHANOL; DECYL GLUCOSIDE; WATER; COCAMIDOPROPYL BETAINE; CURCUMA LONGA (TURMERIC) ROOT EXTRACT; CITRUS LIMON (LEMON) PEEL EXTRACT; KOJIC ACID; TETRASODIUM EDTA

Active ingredient

Rosa Damascena Flower Water

Inactive ingredient

·Water ·Glycerin·Decyl Glucoside·Cocamidopropyl Betaine ·Curcuma Longa (Turmeric) Root Extract·Kojic Acid·Citrus Limon (Lemon) Peel Extract· Phenoxyethanol·Tetrasodium EDTA

Purpose section

1.lt has a deep cleaningeffect, which can efiectivelyremove dirt on the surface ofthe skin and oildeep in thepores, help shrink thepores,and make the skinmore delicate.

2.lt can deeply moisturize theskin, make the skin soft andmoist, and make you fult of youthful vitality.

3.lt can lighten spots, evenout skin tone, reduceblemishes, and make skin brighter.

Banish acne, fade dark spots, and relish silky-smooth skin.

Warning

1).For external use only, avoid directcontact with eyes, lf you feel any
discomfort, stop using itand wash it with plenty of water. In severe cases,
pleaseseek medical attention in time.
2). Not allowed to be used ondamaged skin,

stop use

This product may cause allergic reactions in asmall number of people.
lf youexperience any discomfort,please stop using it immediately.

not use

Not suitable for use by children, pregnantor breast feeding people.

OUT OF CHILDREN

KEEP THE PRODUCT OUT OF REACH OF CHILDREN to

HOW TO USE

Damp face with water andcleanse face with siliconebrush, apply in circulamo-tion. For best results useonce daily, Always applySPF.

Using warm water, massage the pads onto skin in circular motion, leave on for 1-2mins. Rinse off, Follow up with a moisturizer and SPF.

Dosage

take an appropriateamount,Use 2-3 times a week